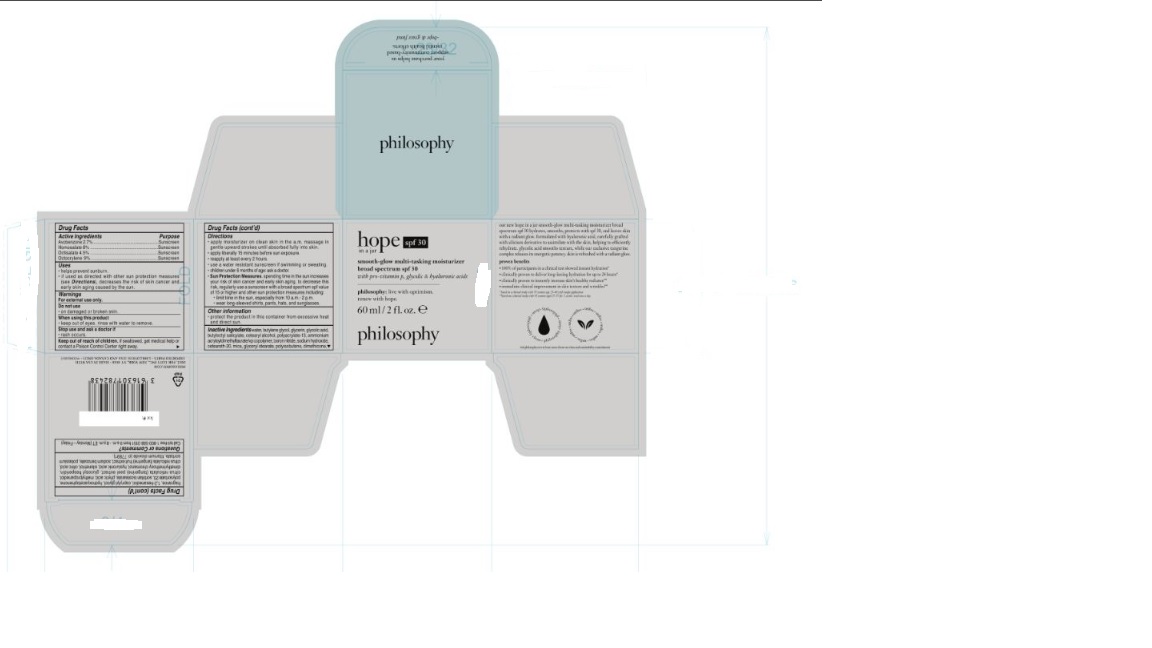 DRUG LABEL: Philosophy Hope in a Jar Smooth-glow Multi-tasking Moisturizer Broad Spectrum SPF 30 with Pro-vitamin P, glycolic and hyaluronic acids
NDC: 50184-0600 | Form: CREAM
Manufacturer: Philosophy, Inc.
Category: otc | Type: HUMAN OTC DRUG LABEL
Date: 20241021

ACTIVE INGREDIENTS: AVOBENZONE 27 mg/1 mL; OCTISALATE 45 mg/1 mL; OCTOCRYLENE 90 mg/1 mL; HOMOSALATE 80 mg/1 mL
INACTIVE INGREDIENTS: CITRIC ACID; 1,3-BUTYLENE GLYCOL 1-MONOMYRISTATE; GLYCERYL STEARATE; FRAGRANCE 13576; CITRUS RETICULATA (TANGERINE) PEEL EXTRACT; DIMETHYLMETHOXY CHROMANOL; SILANETRIOL; HYDROGENATED POLYISOBUTENE (450 MW); HYDROXYACETOPHENONE; SORBITAN ISOSTEARATE; METHYLPROPANEDIOL; POTASSIUM SORBATE; POLYACRYLATE-13; AMMONIUM ACRYLOYLDIMETHYLTAURATE/VP COPOLYMER; PHYTIC ACID; WATER; CETEARYL ALCOHOL; BUTYLOCTYL SALICYLATE; BORON NITRIDE; MICA; CETEARETH-20; DIMETHICONE; HYALURONIC ACID; TITANIUM DIOXIDE; CAPRYLYL GLYCOL; POLYSORBATE 20; GLYCERIN; 1,2-HEXANEDIOL; ECHINACEA PURPUREA FLOWERING TOP WATER; SODIUM HYDROXIDE; GLUCOSYL HESPERIDIN; CITRUS RETICULATA (TANGERINE) FRUIT EXTRACT; SODIUM BENZOATE

Philosophy Hope in a Jar SPF 30

Active Ingredients

Avobenzone 2.7%

Homosalate 8%

Octisalate 4.5%

Octocrylene 9%

Purpose

Sunscreen

Uses

- helps prevent sunburn.
- if used as directed with other sun protection measures (see Directions), decreases the risk of skin cancer and early skin aging cuased by the sun

Warnings

For External use only.

Do not use

- on damaged or broken skin.

When using this product

- keep out of eyes. rinse with water to remove.

Stop use and ask a doctor if

- if rash occurs.

Keep out of reach of children.

if swallowed, get medical help or contact a Poison Control Central right away.

Directions

- appy moisturizer on clean skin in the a.m. massage in gentle upward strokes until absorbed fully into skin.
- apply liberally 15 minutes befoe sun exposure.
- reapply at least every 2 hours.
- use a water resistant sunscreen if swimming or sweating.
- Sun Protection Measures. spending time in the sun increases your risk of skin cancer and early sin aging. to decrease this risk, regularly use a sunscreen with a broad spectrum spf value of 15 or higher and other sun protection measures including:
- limit time in the sun, espcially from 10 a.m.-2 p.m.
- wear long-sleeved shirts, pants, hats, and sunglasses.

Other information

- protect the product in the container from excessive heat and direct sun

Inactive Ingredients

water, butylene glycol, glycerin, glycolic acid, butyloctyl salicylate, cetearyl alcohol, polyacrylate-13, ammoniumacryloyldimethyltaurate/vp copolymer, boron nitride, sodium hydroxide, ceteareth-20, mica, glyceryl stearate, polyisobutene, dimethicone, fragrance, 1,2-hexanediol, caprylyl glycol, hydroxyacetophenone, polysorbate 20, sorbitan isostearate, phytic acid, methylpropanediol, dimethylmethoxy chromanol, hyaluronic acid, silanetriol, citric acid, citrus reticulata (tangerine) fruit extract, sodium benzoate, potassium sorbate, titanium dioxide (CI 77891).

Questions or Comments?

Call toll-free 1-800-568-3151 from 9 a.m. - 8 p.m. ET (Monday - Friday)